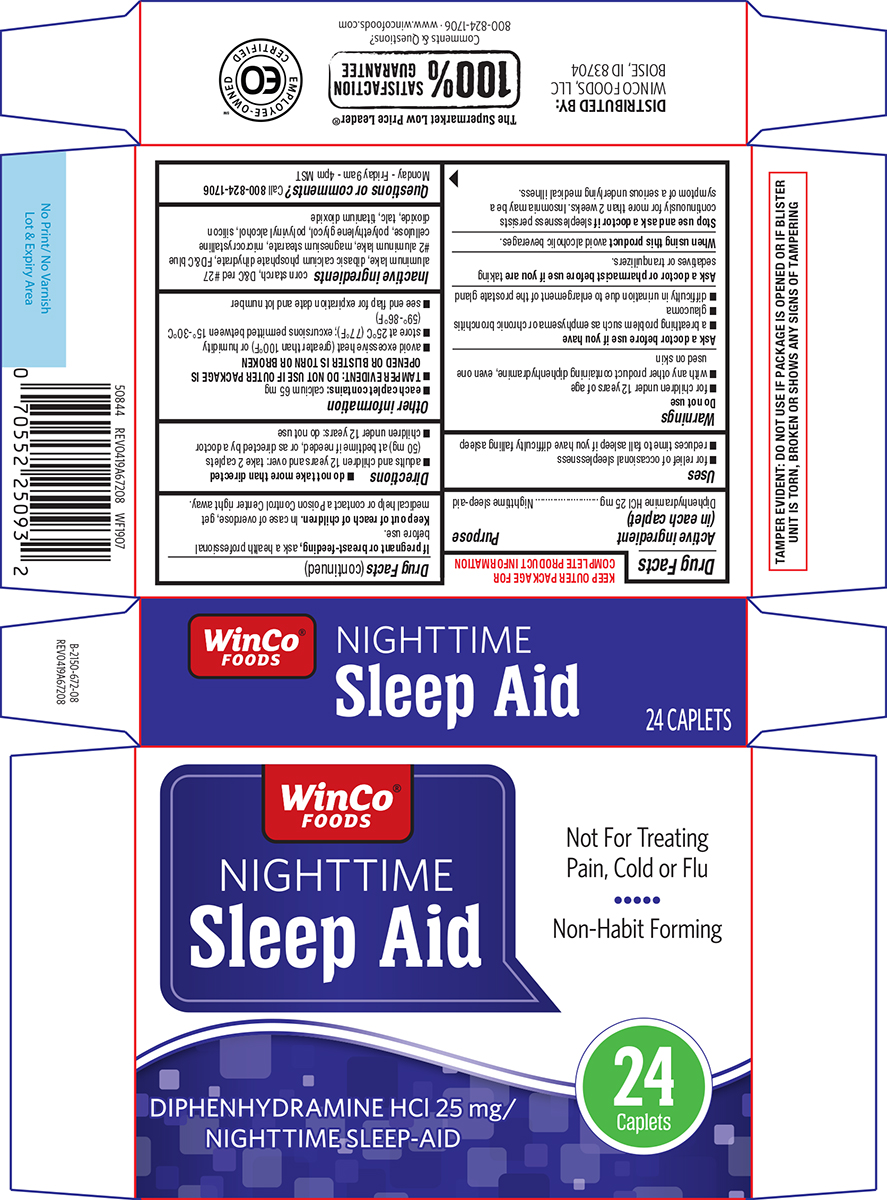 DRUG LABEL: Sleep Aid
NDC: 67091-339 | Form: TABLET, FILM COATED
Manufacturer: WinCo Foods, LLC
Category: otc | Type: HUMAN OTC DRUG LABEL
Date: 20250929

ACTIVE INGREDIENTS: DIPHENHYDRAMINE HYDROCHLORIDE 25 mg/1 1
INACTIVE INGREDIENTS: STARCH, CORN; D&C RED NO. 27 ALUMINUM LAKE; DIBASIC CALCIUM PHOSPHATE DIHYDRATE; FD&C BLUE NO. 2 ALUMINUM LAKE; MAGNESIUM STEARATE; MICROCRYSTALLINE CELLULOSE; POLYETHYLENE GLYCOL, UNSPECIFIED; POLYVINYL ALCOHOL, UNSPECIFIED; SILICON DIOXIDE; TALC; TITANIUM DIOXIDE

Winco 44-672

Active ingredient (in each caplet)

Diphenhydramine HCl 25 mg

Purpose

Nighttime sleep-aid

Uses

- for relief of occasional sleeplessness
- reduces time to fall asleep if you have difficulty falling asleep

Warnings

Do not use

- for children under 12 years of age
- with any other product containing diphenhydramine, even one used on skin

Ask a doctor before use if you have

- a breathing problem such as emphysema or chronic bronchitis
- glaucoma
- difficulty in urination due to enlargement of the prostate gland

Ask a doctor or pharmacist before use if you are

taking sedatives or tranquilizers.

When using this product

avoid alcoholic beverages.

Stop use and ask a doctor if

sleeplessness persists continuously for more than 2 weeks. Insomnia may be a symptom of a serious underlying medical illness.

If pregnant or breast-feeding,

ask a health professional before use.

Keep out of reach of children.

In case of overdose, get medical help or contact a Poison Control Center right away.

Directions

- do not take more than directed
- adults and children 12 years and over: take 2 caplets (50 mg) at bedtime if needed, or as directed by a doctor
- children under 12 years: do not use

Other information

- each caplet contains: calcium 65 mg
- TAMPER EVIDENT: DO NOT USE IF OUTER PACKAGE IS OPENED OR BLISTER IS TORN OR BROKEN
- avoid excessive heat (greater than 100°F) or humidity
- store at 25°C (77°F); excursions permitted between 15°-30°C (59°-86°F)
- see end flap for expiration date and lot number

Inactive ingredients

corn starch, D&C red #27 aluminum lake, dibasic calcium phosphate dihydrate, FD&C blue #2 aluminum lake, magnesium stearate, microcrystalline cellulose, polyethylene glycol, polyvinyl alcohol, silicon dioxide, talc, titanium dioxide

Questions or comments?

Call 800-824-1706 Monday - Friday 9am - 4pm MST

Principal display panel

WinCo®
FOODS

NIGHTTIME
Sleep Aid

DIPHENHYDRAMINE HCl 25 mg/
NIGHTTIME SLEEP-AID

Not for Treating
Pain, Cold or Flu

Non-Habit Forming

24
Caplets

TAMPER EVIDENT: DO NOT USE IF PACKAGE IS OPENED OR IF BLISTER
UNIT IS TORN, BROKEN OR SHOWS ANY SIGNS OF TAMPERING

DISTRIBUTED BY:
WINCO FOODS, LLC
BOISE, ID 83704

The Supermarket Low Price Leader®

100% SATISFACTION GUARANTEE
Comments & Questions?
800-824-1706 www.wincofoods.com

50844 REV0419A67208 WF1907

Winco 44-672